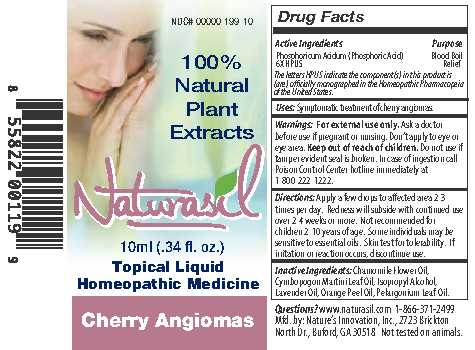 DRUG LABEL: Naturasil
NDC: 10893-120 | Form: LIQUID
Manufacturer: Nature's Innovation
Category: homeopathic | Type: HUMAN OTC DRUG LABEL
Date: 20210114

ACTIVE INGREDIENTS: PHOSPHORIC ACID 6 [hp_X]/1 1
INACTIVE INGREDIENTS: CHAMOMILE FLOWER OIL; PALMAROSA OIL; ISOPROPYL ALCOHOL; LAVENDER OIL; ORANGE OIL; GERANIUM OIL, ALGERIAN TYPE

Cherry Angiomas 10 ml

Drug Facts

Active Ingredients

Phosphoricum Acidum (Phosphoric Acid)

6X HPUS

DESCRIPTION

The letters HPUS indicate the component(s) in this product is (are) officially monographed in the Homeopathic Pharmacopeia of the United States.

Purpose

Blood Boil Relief

INDICATIONS AND USAGE

Uses: Symptomatic treatment of cherry angiomas.

Warnings: For external use only.

Ask a doctor before use if pregnant or nursing.

OTHER SAFETY INFORMATION

Don't apply to eye or eye area.

Keep out of reach of children.

Do not use if tamper evident seal is broken.

OTHER SAFETY INFORMATION

In case of ingestion call Poison Control Center hotline immediately at 1-800-222-1222.

DOSAGE AND ADMINISTRATION

Directions: Apply a few drops to affected area 2-3 times per day. Redness will subside with continued use over 2-4 weeks or more. Not recommended for children 2-10 years of age. Some individuals may be sensitive to essential oils. Skin test for tolerability. If irritation or reaction occurs, discontinue use.

INACTIVE INGREDIENT

Inactive Ingredients: Chamomile Flower Oil, Cymbopogon Martini Leaf Oil, Isopropyl Alcohol, Lavender Oil, Orange Peel Oil, Pelargonium Leaf Oil.

Questions? www.naturasil.com 1-866-371-2499

Mfd. by: Nature's Innovation, Inc., 2723 Brickton

North Dr., Buford, GA 30518 Not tested on animals.

PACKAGE LABEL

100% Natural Plant Extracts

Naturasil

10ml (.34 fl. oz.)

Topical Liquid

Homeopathic Medicine

Cherry Angiomas